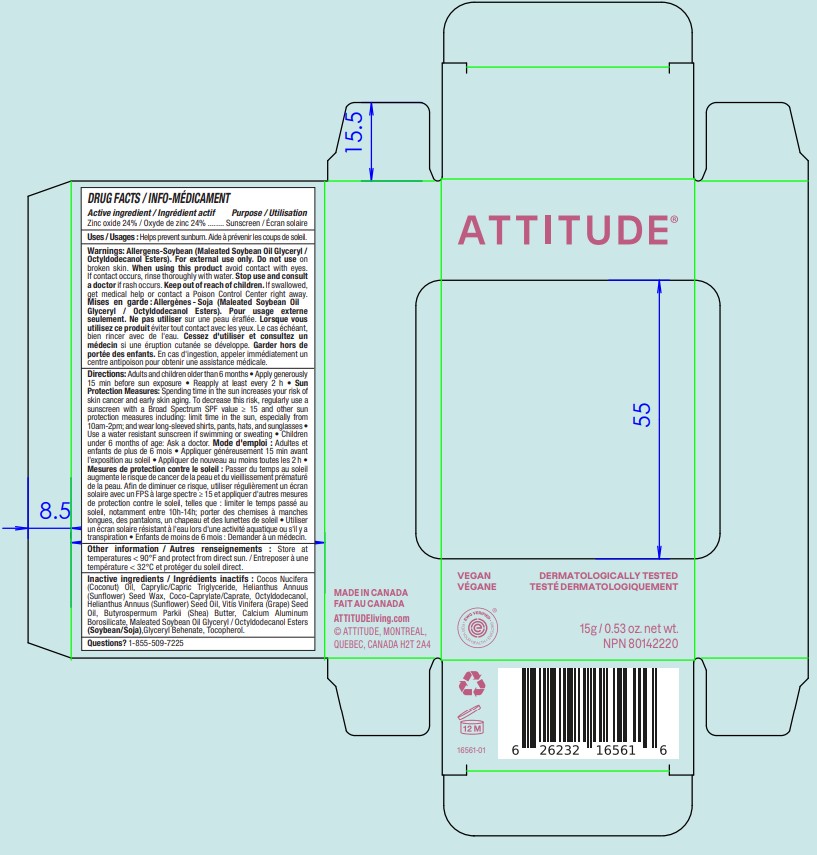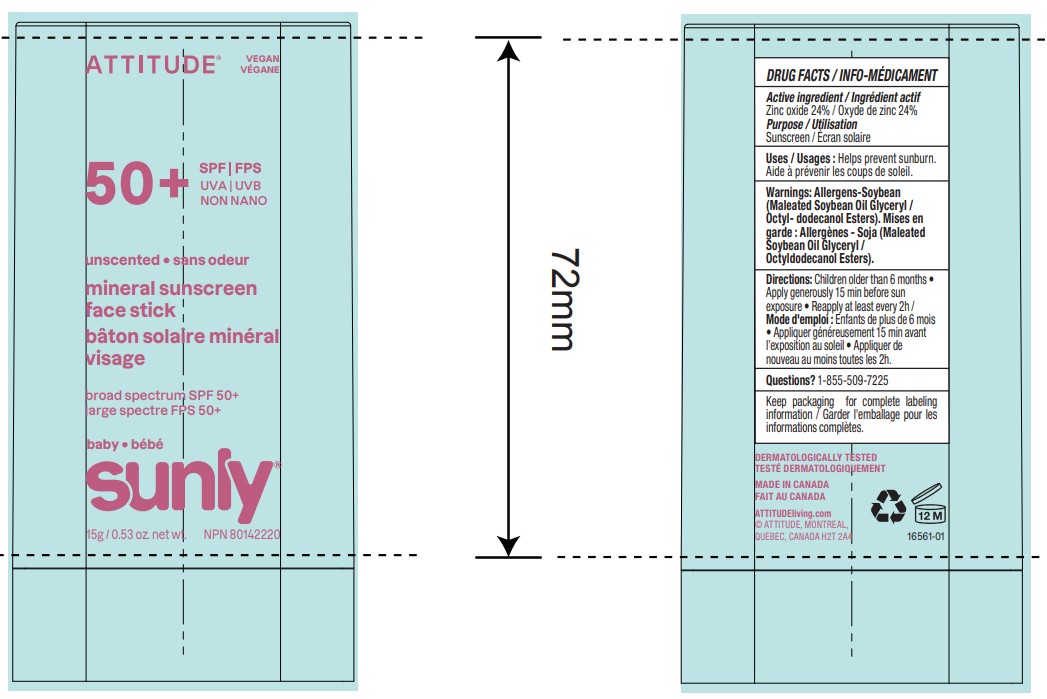 DRUG LABEL: ATTITUDE Sunly Baby Mineral Sunscreen Face Stick SPF 50 Unscented
NDC: 61649-561 | Form: STICK
Manufacturer: 9055-7588 Québec Inc.DBA ATTITUDE
Category: otc | Type: HUMAN OTC DRUG LABEL
Date: 20251203

ACTIVE INGREDIENTS: ZINC OXIDE 24 g/100 g
INACTIVE INGREDIENTS: CAPRYLIC/CAPRIC TRIGLYCERIDE; VITIS VINIFERA (GRAPE) SEED OIL; COCO-CAPRYLATE/CAPRATE; HELIANTHUS ANNUUS (SUNFLOWER) SEED WAX; HELIANTHUS ANNUUS (SUNFLOWER) SEED OIL; OCTYLDODECANOL; BUTYROSPERMUM PARKII (SHEA) BUTTER; COCOS NUCIFERA (COCONUT) OIL; MALEATED SOYBEAN OIL GLYCERYL/OCTYLDODECANOL ESTERS; GLYCERYL DIBEHENATE; CALCIUM ALUMINUM BOROSILICATE; TOCOPHEROL

ATTITUDE Sunly Baby Mineral Sunscreen Face Stick SPF 50 Unscented

DRUG FACTS

ACTIVE INGREDIENT

Zinc oxide (24 %)

PURPOSE

Sunscreen

INDICATIONS AND USAGE

Helps prevent sunburn

WARNINGS

For external use only.

Do not use on broken skin.

When using this product avoid contact with eyes. If contact occurs, rinse thoroughly with water.

Keep out of reach of children. If swallowed, get medical help or contact a Poison Control Center right away.

OTHER SAFETY INFORMATION

Allergens-Soybean (Maleated Soybean Oil Glyceryl / Octyldodecanol Esters).

Stop use and consult a doctor if rash occurs.

DOSAGE AND ADMINISTRATION

Adults and children older than 6 months • Apply generously 15 min before sun exposure • Reapply at least every 2 h • Sun Protection Measures: Spending time in the sun increases your risk of skin cancer and early skin aging. To decrease this risk, regularly use a sunscreen with a Broad Spectrum SPF value ≥ 15 and other sun protection measures including: limit time in the sun, especially from 10am-2pm; and wear long-sleeved shirts, pants, hats, and sunglasses • Use a water resistant sunscreen if swimming or sweating • Children under 6 months of age: Ask a doctor.

INACTIVE INGREDIENT

Cocos Nucifera (Coconut) Oil, Caprylic/Capric Triglyceride, Helianthus Annuus (Sunflower) Seed Wax, Coco-Caprylate/Caprate, Octyldodecanol, Helianthus Annuus (Sunflower) Seed Oil, Vitis Vinifera (Grape) Seed Oil, Butyrospermum Parkii (Shea) Butter, Calcium Aluminum Borosilicate, Maleated Soybean Oil Glyceryl / Octyldodecanol Esters (Soybean/Soja),Glyceryl Behenate, Tocopherol.

STORAGE AND HANDLING

Store at temperatures < 90F and protect from direct sun.

Questions ? 1-855-509-7225

PACKAGE LABEL

ATTITUDE

EWG Verified

VEGAN

SPF 50+

UVA ¦ UVB

NON NANO

unscented

mineral sunscreen face stick

Broad spectrum SPF 50+

baby

sunly

15 g / 0.53 oz. net wt.

NPN 80142220

Made in Canada

Dermatologically tested